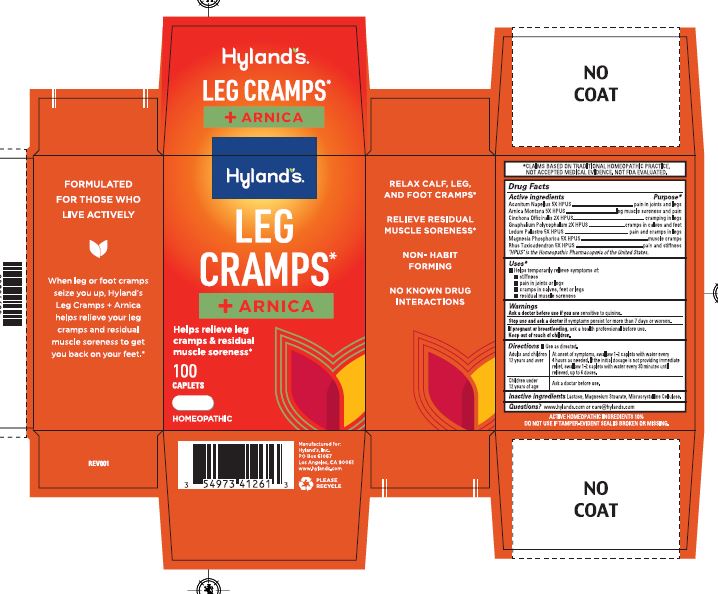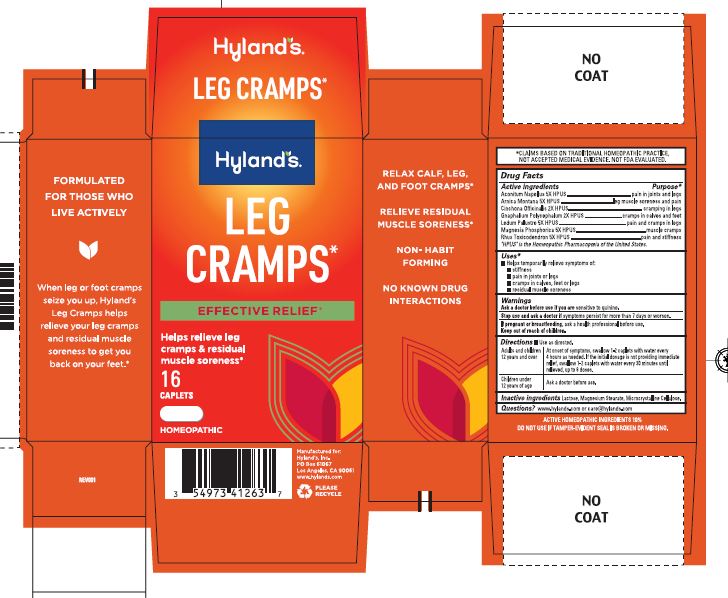 DRUG LABEL: Hylands Leg Cramps With Arnica
NDC: 54973-4126 | Form: TABLET
Manufacturer: Hyland's Consumer Health Inc.
Category: homeopathic | Type: HUMAN OTC DRUG LABEL
Date: 20250702

ACTIVE INGREDIENTS: TOXICODENDRON PUBESCENS LEAF 5 [hp_X]/1 1; CINCHONA BARK 2 [hp_X]/1 1; PSEUDOGNAPHALIUM OBTUSIFOLIUM 2 [hp_X]/1 1; LEDUM PALUSTRE TWIG 2 [hp_X]/1 1; ARNICA MONTANA WHOLE 5 [hp_X]/1 1; ACONITUM NAPELLUS 5 [hp_X]/1 1
INACTIVE INGREDIENTS: LACTOSE MONOHYDRATE; MAGNESIUM STEARATE; CELLULOSE, MICROCRYSTALLINE

LEG CRAMPS WITH ARNICA CAPLETS

Homeopathic claims

*CLAIMS BASED ON TRADITIONAL HOMEOPATHICPRACTICE,

NOT ACCEPTED MEDICAL EVIDENCE, NOT FDA EVALUATED.

DRUG FACTS

Active Ingredients

ACONITUM NAPELLUS 5X HPUS

ARNICA MONTANA 5X HPUS

CINCHONA OFFICINALIS 2X HPUS

GNAPHALIUM POLYCEPHALIUM 2X HPUS

LEDUM PAULSTRE 5X HPUS

MAGNESIA PHOSPHORICA 5X HPUS

RHUS TOXICODENDRON 5X HPUS

"HPUS" is the Homeopathic Pharmacopeia of the United States

Purpose*

Pain in joints and legs

Leg muscle soreness and pain

Cramping in legs

Cramps in calves and feet

Pain and cramps in legs

Muscle cramps

Pain and stiffness

Uses*

Helps temporarily relieve symptoms of:

- Stiffness
- Pain in joints or legs
- Cramps in calves, feet or legs
- Residuall muscle soreness

Directions

Use as directed

Adults and children 12 and over:

At onset of symptoms, swallow 1-2 caplets with water every 4 hours as needed. If the initial dosage is not providing immediate relief, swallow 1-2 caplets with water every 30 minutes until relieved, up to 6 doses.

Children under 12 years of age:

Ask a doctor beofre use

Inactive ingredients

Lactose, Magnesium Stearate, Microcrystalline Cellulose

Questions?

www.hylands.com or care@hylands.com

DOSAGE AND ADMINISTRATION

Oral

KEEP OUT OF REACH OF CHILDREN

ASK A DOCTOR BEFORE USE IF:

SENSITIVE TO QUININE

PREGNANT OR BREASTFEEDING

PACKAGE LABEL

Hylands Naturals

Leg Cramps*

+Arnica

Helps relieve leg

cramps and residual soreness

100

caplets

Homeopathic